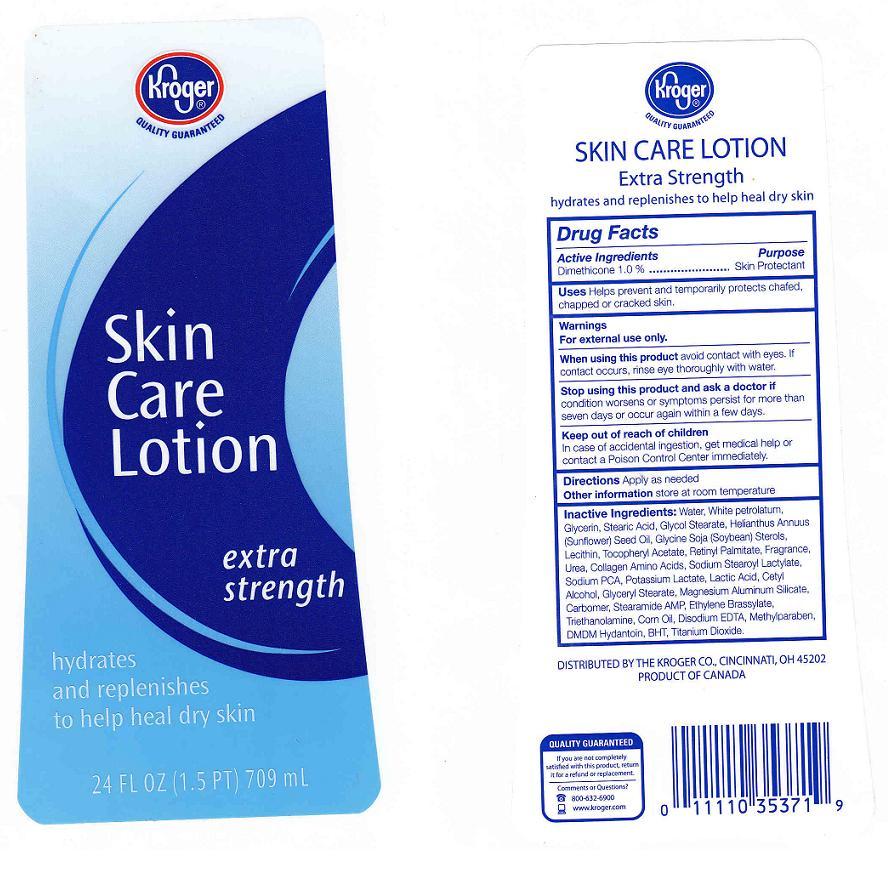 DRUG LABEL: SKIN CARE LOTION
NDC: 59450-310 | Form: LOTION
Manufacturer: THE KROGER CO
Category: otc | Type: HUMAN OTC DRUG LABEL
Date: 20100625

ACTIVE INGREDIENTS: DIMETHICONE 1.0000 mL/100 mL

SKIN CARE LOTION

ACTIVE INGREDIENT

DIMETHICONE 1.0% (SKIN PROTECTANT)

WARNING

FOR EXTERNAL USE ONLY.

WHEN USING

AVOID CONTACT WITH EYES, IF CONTACT OCCURS, RINSE EYE THROUGHLY WITH WATER.

STOP USING THIS PRODUCT AND ASK A DOCTOR IF

CONDITION WORSENS OR SYMPTOMS PERSIST FOR MORE THAN SEVEN DAYS OR OCCUR AGAIN WITHIN A FEW DAYS.

KEEP OUT OF REACH OF CHILDREN

IN CASE OF ACCIDENTAL INGESTION, GET MEDICAL HELP OR CONTACT A POISON CONTROL CENTER IMMEDIATELY.

USES

HELPS PREVENT AND TEMPORARILY PROTECTS CHAFED, CHAPPED OR CRACKED SKIN.

FRONT AND BACK LABELS

24OZ FRONT AND BACK LABELS: K24.jpg